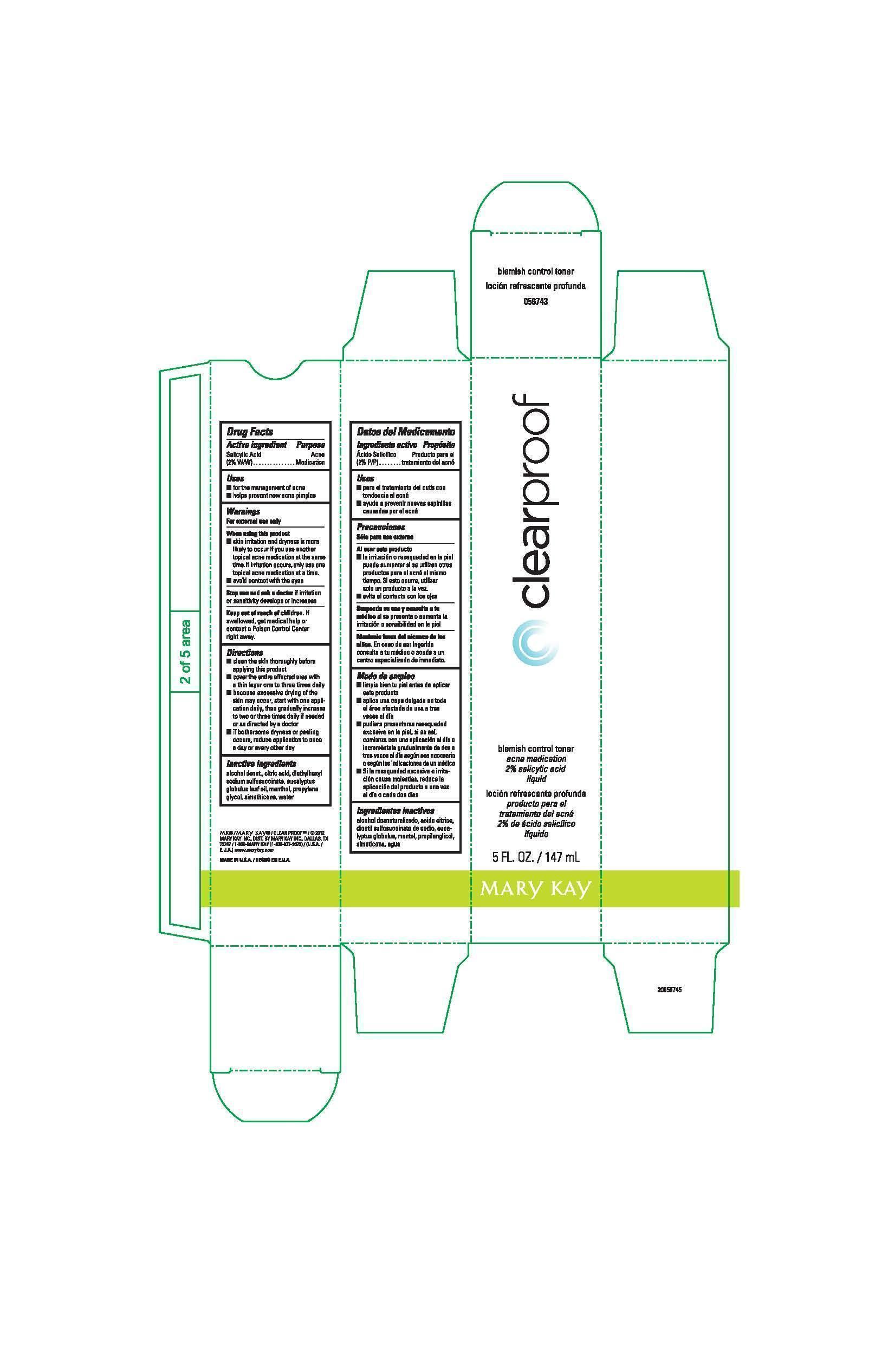 DRUG LABEL: Clear Proof Blemish Control Toner
NDC: 51531-6743 | Form: LIQUID
Manufacturer: Mary Kay Inc.
Category: otc | Type: HUMAN OTC DRUG LABEL
Date: 20241217

ACTIVE INGREDIENTS: SALICYLIC ACID 2 g/100 mL
INACTIVE INGREDIENTS: WATER; ALCOHOL; DENATONIUM BENZOATE; TERT-BUTYL ALCOHOL; PROPYLENE GLYCOL; CITRIC ACID MONOHYDRATE; DOCUSATE SODIUM; EUCALYPTUS OIL; MENTHOL; DIMETHICONE; SILICON DIOXIDE

Clear Proof Blemish Control Toner
Drug Facts

Active ingredient

Salicylic Acid (2% W/W)

Purpose

Acne Medication

Uses

- for the management of acne
- helps prevent new acne pimples

Warnings

For external use only

When using this product

- skin irritation and dryness is more likely to occur if you use another topical acne medication at the same time. If irritation occurs, only use one topical acne medication at a time.
- avoid contact with the eyes

Stop use and ask a doctor

if irritation or sensitivity develops or increases

Keep out of reach of children.

If swallowed, get medical help or contact a Poison Control Center right away.

Directions

- clean the skin thoroughly before applying this product
- cover the entire affected area with a thin layer one to three times daily
- because excessive drying of the skin may occur, start with one application daily, then gradually increase to two or three times daily if needed or as directed by a doctor
- if bothersome dryness or peeling occurs, reduce application to once a day or every other day

Inactive ingredients

alcohol denat., citric acid, diethylhexyl sodium sulfosuccinate, eucalyptus globulus leaf oil, menthol, propylene glycol, simethicone, water

Principal Display Panel - 147 mL bottle

clearproof

blemish control toner

acne medication

2% salicylic acid

liquid

5 FL. OZ. / 147 mL

Mary Kay